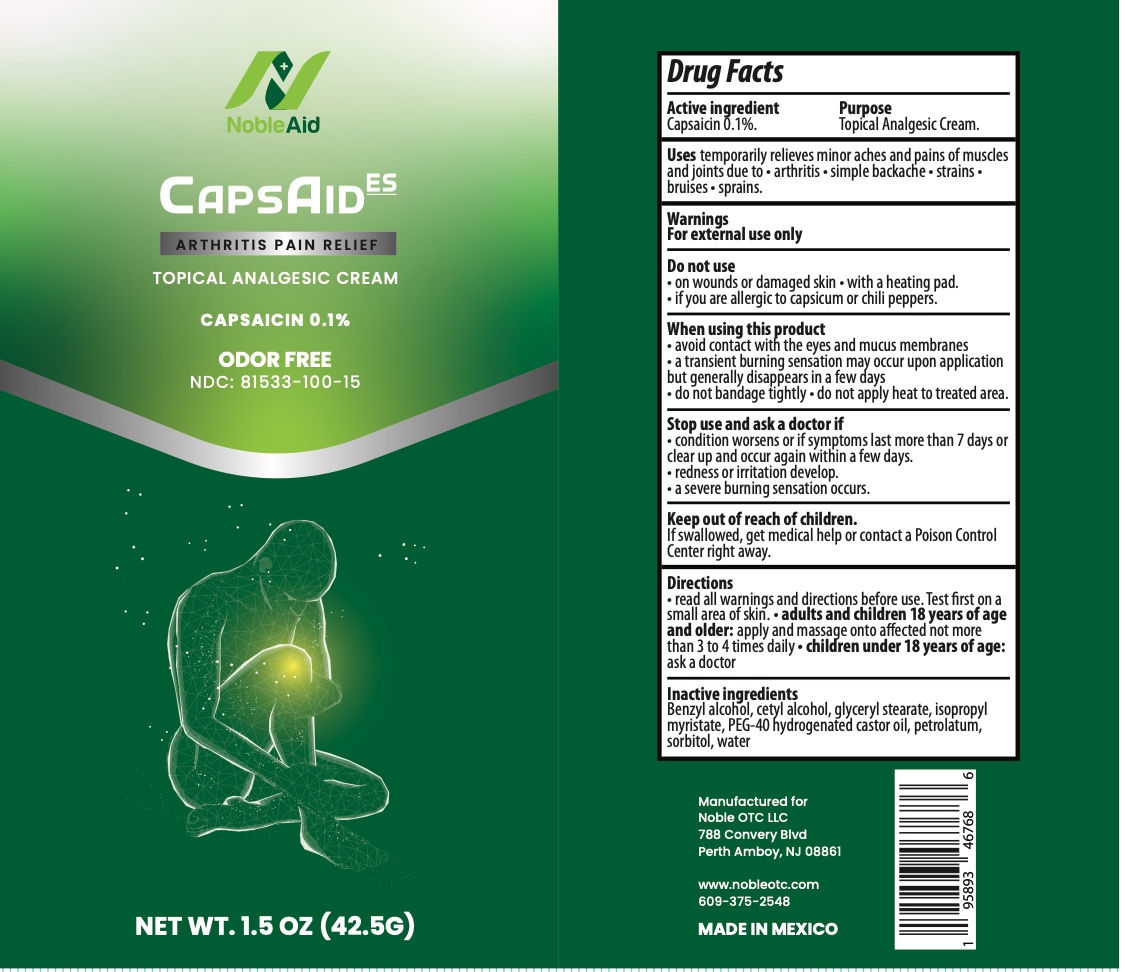 DRUG LABEL: NobleAid CapsAid
NDC: 81533-100 | Form: CREAM
Manufacturer: Noble OTC LLC
Category: otc | Type: HUMAN OTC DRUG LABEL
Date: 20211007

ACTIVE INGREDIENTS: CAPSAICIN 0.1 g/100 g
INACTIVE INGREDIENTS: ISOPROPYL MYRISTATE; PETROLATUM; BENZYL ALCOHOL; CETYL ALCOHOL; GLYCERYL MONOSTEARATE; SORBITOL; WATER; POLYOXYL 40 HYDROGENATED CASTOR OIL

NobleAid CapsAid Cream

Drug Facts

Active ingredient

Capsaicin 0.1%.

Purpose

Topical Analgesic Cream.

INDICATIONS AND USAGE

Uses temporarily relieves minor aches and pains of muscles adn joints due to

- arthritis
- simple backache
- strains
- bruises
- sprains

Warnings

For external use only

Do not use

- on wounds or damaged skin
- with a heating pad
- if you are allergic to capsicum or chili peppers

When using this product

- avoid contact with the eyes and mucus membranes
- a transient burning sensation may occur upon application but generally disappears in a few days
- do not bandage tightly
- do not apply heat to treated area

Stop use and ask a doctor if

- condition worsens or if symptoms last more than 7 day or clear up and occur again within a few days.
- redness or irritation develop.
- a severe burning sensation occurs.

Keep out of reach of children.

If swallowed, get medical help or contact a Poison Control Center right away.

Directions

- read all warnings adn directions before use. Test first on a small area of skin.
- adults and children 18 years of age and older: apply adn massage on to affected area not more than 3 to 4 times daily
- children under 18 years of age: ask a doctor

Inactive ingredienta:

Benzyl alcohol, cetyl alcohol, glyceryl stearate, isopropyl myristate, PEG-40 hydrogenated castor oil, petrolatum, sorbitol, water

Manufactured for

Noble OTC LLC

788 Convery Blvd

Perth Amboy, NJ 08861

www.nobleotc.com

609-375-2548

MADE IN MEXICO

PACKAGE LABEL

NobleAid

CapsAid ES

ARTHRITIS PAIN RELIEF

TOPICAL ANALGESIC CREAM

CAPSAICIN 0.1%

ODOR FREE

NDC: 81533-100-15

NET WT. 1.5 OZ (42.5G)